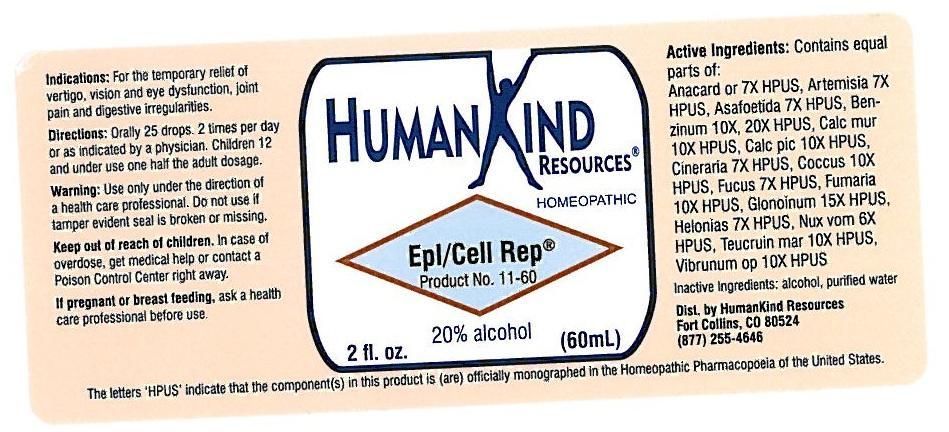 DRUG LABEL: Epl-Cell Repair
NDC: 64616-089 | Form: LIQUID
Manufacturer: Vitality Works, Inc.
Category: homeopathic | Type: HUMAN OTC DRUG LABEL
Date: 20251217

ACTIVE INGREDIENTS: ASAFETIDA 7 [hp_X]/1 mL; BENZENE 20 [hp_X]/1 mL; CALCIUM CHLORIDE 10 [hp_X]/1 mL; CALCIUM PICRATE 10 [hp_X]/1 mL; JACOBAEA MARITIMA 7 [hp_X]/1 mL; PROTORTONIA CACTI 10 [hp_X]/1 mL; FUCUS VESICULOSUS 7 [hp_X]/1 mL; NITROGLYCERIN 15 [hp_X]/1 mL; CHAMAELIRIUM LUTEUM ROOT 7 [hp_X]/1 mL; STRYCHNOS NUX-VOMICA SEED 6 [hp_X]/1 mL; TEUCRIUM MARUM 10 [hp_X]/1 mL; VIBURNUM OPULUS BARK 10 [hp_X]/1 mL; FUMARIA OFFICINALIS FLOWERING TOP 8 [hp_X]/1 mL; SEMECARPUS ANACARDIUM JUICE 7 [hp_X]/1 mL; ARTEMISIA VULGARIS ROOT 7 [hp_X]/1 mL
INACTIVE INGREDIENTS: ALCOHOL; WATER

Epl/Cell

Epl/Cell Repair

Anacardium Orientale 7X Calcarea Picrata 10X Glonoinum 15X

Artemisia Vulgaris 7X Cineraria Maritima 7X Helonias Dioica 7X

Asafoetida 7X Coccus Cacti 10X Nux Vomica 6X

Benzinum 10X, 20X Fucus Vesiculosus 7X Teucrium Marum 10X

Calcarea Muriatica 10X Fumaria Officinalis 10X Viburnum Opul 10X

Epl/Cell Repair

Alcohol, Purified Water

Epl/Cell Repair

Use only under the direction of a health care professional. Do not use if tamper evident seal is broken or missing.

Epl/Cell Repair

Keep out of reach of children. In case of overdose, get medical help or contact a Poison Control Center right away.

Epl/Cell Repair

For the tmporary relief of vertigo, vision and eye dysfunction, joint pain and digestive irregularities.

Epl/Cell Repair

Orally 25 drops, 2 times per day or as indicated by a physician. Children 12 and under use one half the adult dosage.

Epl/Cell Repair

Eases vertigo, vision and eye dysfunction, joint pain and digestive irregularities.